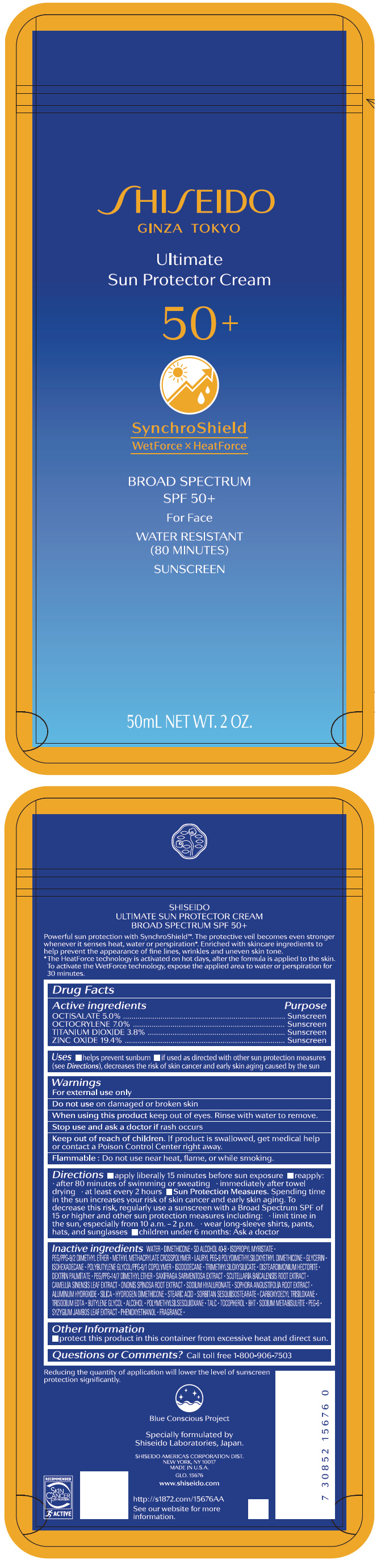 DRUG LABEL: SHISEIDO ULTIMATE SUN PROTECTOR
NDC: 58411-480 | Form: CREAM
Manufacturer: SHISEIDO AMERICAS CORPORATION
Category: otc | Type: HUMAN OTC DRUG LABEL
Date: 20260105

ACTIVE INGREDIENTS: OCTISALATE 3.105 g/50 mL; TITANIUM DIOXIDE 2.359 g/50 mL; OCTOCRYLENE 4.347 g/50 mL; ZINC OXIDE 12.047 g/50 mL
INACTIVE INGREDIENTS: WATER; DIMETHICONE; ISOPROPYL MYRISTATE; PEG/PPG-9/2 DIMETHYL ETHER; METHYL METHACRYLATE/GLYCOL DIMETHACRYLATE CROSSPOLYMER; LAURYL PEG-9 POLYDIMETHYLSILOXYETHYL DIMETHICONE; GLYCERIN; ISOHEXADECANE; ISODODECANE; TRIMETHYLSILOXYSILICATE (M/Q 0.6-0.8); DISTEARDIMONIUM HECTORITE; DEXTRIN PALMITATE (CORN; 20000 MW); PEG/PPG-14/7 DIMETHYL ETHER; SAXIFRAGA STOLONIFERA LEAF; SCUTELLARIA BAICALENSIS ROOT; GREEN TEA LEAF; ONONIS SPINOSA ROOT; HYALURONATE SODIUM; SOPHORA FLAVESCENS ROOT; ALUMINUM HYDROXIDE; SILICON DIOXIDE; HYDROGEN DIMETHICONE (13 CST); STEARIC ACID; SORBITAN SESQUIISOSTEARATE; EDETATE TRISODIUM; BUTYLENE GLYCOL; ALCOHOL; POLYMETHYLSILSESQUIOXANE (4.5 MICRONS); TALC; .ALPHA.-TOCOPHEROL; BUTYLATED HYDROXYTOLUENE; SODIUM METABISULFITE; POLYETHYLENE GLYCOL 300; SYZYGIUM JAMBOS LEAF; PHENOXYETHANOL; SODIUM POLYMETAPHOSPHATE; .ALPHA.-CELLULOSE; FERRIC OXIDE RED; FERRIC OXIDE YELLOW; FERROSOFERRIC OXIDE

SHISEIDO ULTIMATE SUN PROTECTOR CREAM

Drug Facts

ACTIVE INGREDIENT

Active ingredients | Purpose
Octisalate 5.0% | Sunscreen
Octocrylene 7.0% | Sunscreen
Titanium Dioxide 3.8% | Sunscreen
Zinc Oxide 19.4% | Sunscreen

Uses

- helps prevent sunburn
- if used as directed with other sun protection measures (see Directions), decreases the risk of skin cancer and early skin aging caused by the sun

Warnings

For external use only

Do not use on damaged or broken skin

WHEN USING

When using this productkeep out of eyes. Rinse with water to remove.

Stop use and ask a doctorif rash occurs.

Keep out of reach of children.If product is swallowed, get medical help or contact a Poison Control Center right away.

Flammable

Do not use near heat, flame, or while smoking.

Directions

For sunscreen use:

- apply liberally 15 minutes before sun exposure
- reapply:
  - after 80 minutes of swimming or sweating
  - immediately after towel drying
  - at least every two hours
- Sun Protection Measures. Spending time in the sun increases your risk of skin cancer and early skin aging. To decrease this risk, regularly use a sunscreen with a broad spectrum SPF of 15 or higher and other sun protection measures including:
  - limit time in the sun, especially from 10 a.m. – 2 p.m.
  - wear long-sleeve shirts, pants, hats, and sunglasses
  - children under 6 months: Ask a doctor

Inactive Ingredients

WATER▪DIMETHICONE▪SD ALCOHOL 40-B▪ISOPROPYL MYRISTATE▪PEG/PPG-9/2 DIMETHYL ETHER▪METHYL METHACRYLATE CROSSPOLYMER▪LAURYL PEG-9 POLYDIMETHYLSILOXYETHYL DIMETHICONE▪GLYCERIN▪ISOHEXADECANE▪POLYBUTYLENE GLYCOL/PPG-9/1 COPOLYMER▪ISODODECANE▪TRIMETHYLSILOXYSILICATE▪DISTEARDIMONIUM HECTORITE▪DEXTRIN PALMITATE▪PEG/PPG-14/7 DIMETHYL ETHER▪SAXIFRAGA SARMENTOSA EXTRACT▪SCUTELLARIA BAICALENSIS ROOT EXTRACT▪CAMELLIA SINENSIS LEAF EXTRACT▪ONONIS SPINOSA ROOT EXTRACT▪SODIUM HYALURONATE▪SOPHORA ANGUSTIFOLIA ROOT EXTRACT▪ALUMINUM HYDROXIDE▪SILICA▪HYDROGEN DIMETHICONE▪STEARIC ACID▪SORBITAN SESQUIISOSTEARATE▪CARBOXYDECYL TRISILOXANE▪TRISODIUM EDTA▪BUTYLENE GLYCOL▪ALCOHOL▪POLYMETHYLSILSESQUIOXANE▪TALC▪TOCOPHEROL▪BHT▪SODIUM METABISULFITE▪PEG-6▪SYZYGIUM JAMBOS LEAF EXTRACT▪PHENOXYETHANOL▪FRAGRANCE▪

Other information

Protect this product in this container from excessive heat and direct sun.

Questions or comments?

Call toll free 1-800-906-7503

PRINCIPAL DISPLAY PANEL - 50 mL Tube Label

SHISEIDO
GINZA TOKYO

Ultimate
Sun Protector Cream

50+

SynchroShield
WetForce × HeatForce

BROAD SPECTRUM
SPF 50+

For Face

WATER RESISTANT
(80 MINUTES)

SUNSCREEN

50mL NET WT. 2 OZ.